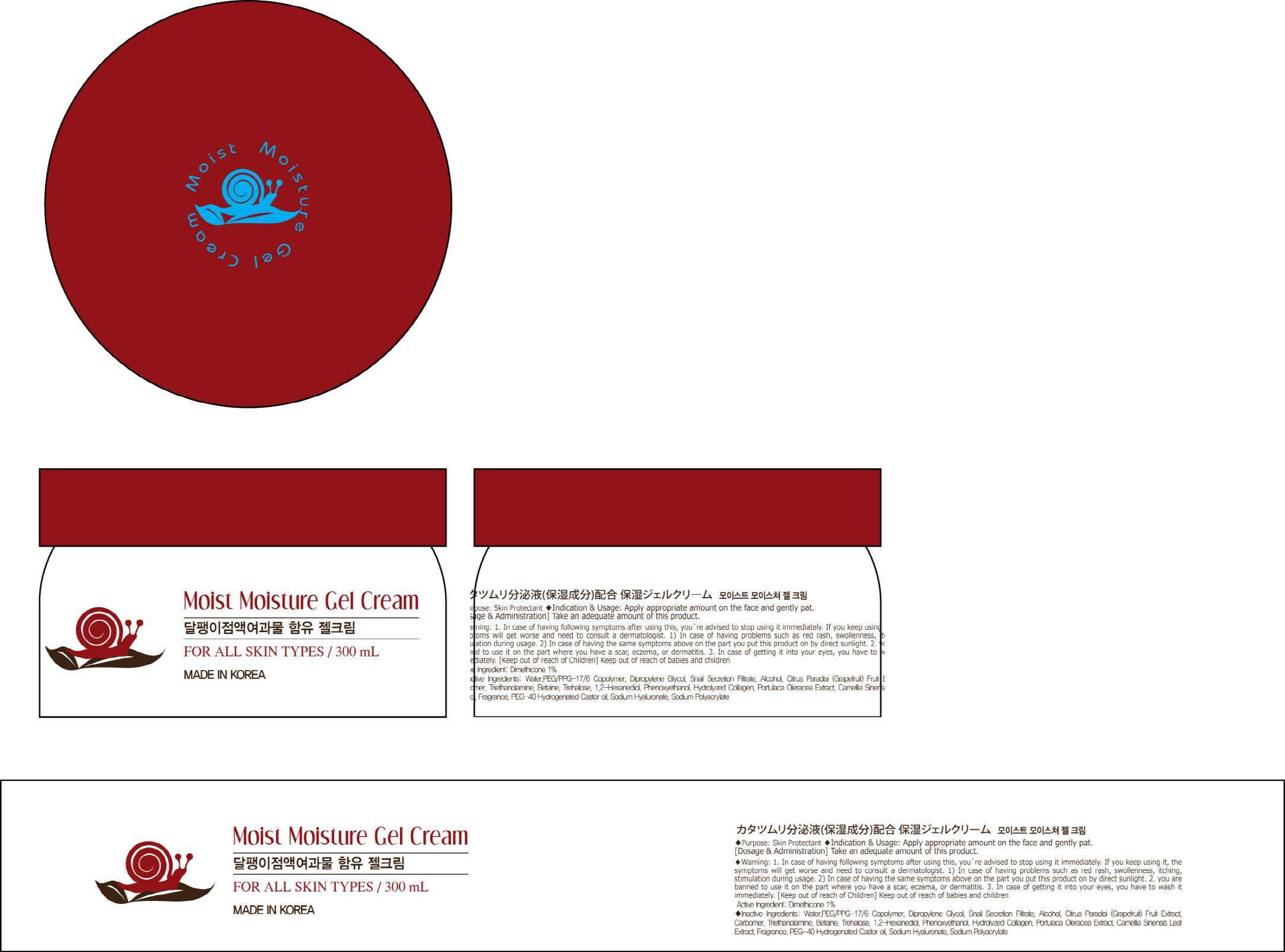 DRUG LABEL: MOIST MOISTURE
NDC: 69072-040 | Form: CREAM
Manufacturer: Seindni Co.,ltd
Category: otc | Type: HUMAN OTC DRUG LABEL
Date: 20181210

ACTIVE INGREDIENTS: Dimethicone 3 mg/300 mL
INACTIVE INGREDIENTS: Water; Dipropylene Glycol

ACTIVE INGREDIENT

Active Ingredients: Dimethicone 1%

INACTIVE INGREDIENT

Inactive Ingredients:
Water,PEG/PPG-17/6 Copolymer,Dipropylene Glycol,Snail Secretion Filtrate,Alcohol,Citrus Paradisi (Grapefruit) Fruit Extract,Carbomer,Triethanolamine,Betaine,Trehalose,1,2-Hexanediol,Phenoxyethanol, Hydrolyzed Collagen,Portulaca Oleracea Extract,Camellia Sinensis Leaf Extract,Fragrance,PEG-40 Hydrogenated Castor oil,Sodium Hyaluronate,Sodium Polyacrylate

PURPOSE

Purpose: Skin Protectant

WARNINGS

Warning:
1. In case of having following symptoms after using this, you're advised to stop using it immediately. If you keep using it, the symptoms will get worse and need to consult a dermatologist. 1) In case of having problems such as red rash, swollenness, itching, stimulation during usage. 2) In case of having the same symptoms above on the part you put this product on by direct sunlight. 2. you are banned to use it on the part where you have a scar, eczema, or dermatitis. 3. In case of getting it into your eyes, you have to wash it immediately.

Keep out of reach of Children: Keep out of reach of babies and children

INDICATIONS AND USAGE

Indication and Usage: Apply appropriate amount on the face and gently pat.

Dosage and Administration : Take an adequate amount of this product.